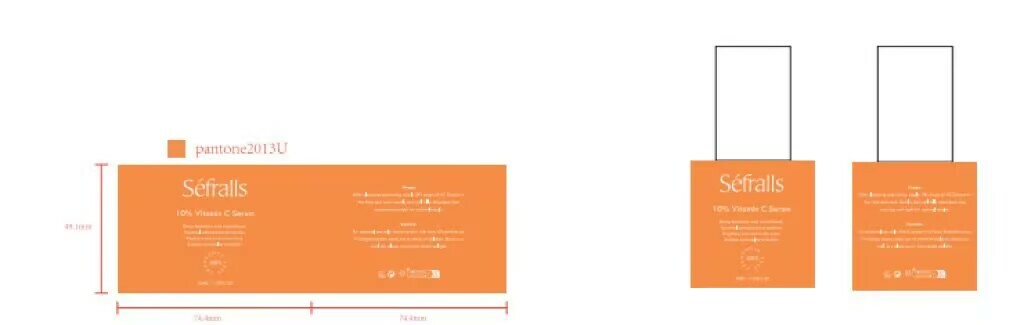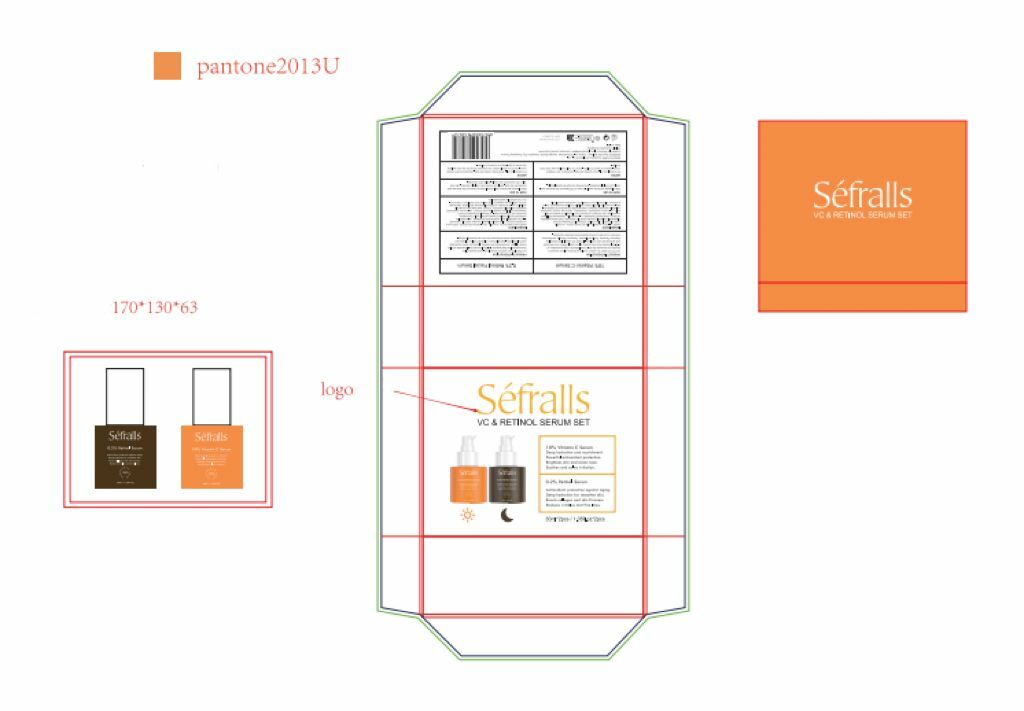 DRUG LABEL: 2-Pack Facial Serum
NDC: 84148-011 | Form: LIQUID
Manufacturer: Guangzhou Ariel Biotech Co., Ltd.
Category: otc | Type: HUMAN OTC DRUG LABEL
Date: 20241125

ACTIVE INGREDIENTS: WATER 78.894 g/100 mL; TARAXACUM OFFICINALE LEAF 0.01 g/100 mL; LAVANDULA ANGUSTIFOLIA (LAVENDER) OIL 0.03 g/100 mL; PURSLANE 0.07 g/100 mL; 3-O-ETHYL ASCORBIC ACID 8 g/100 mL
INACTIVE INGREDIENTS: C20-22 ALKYL PHOSPHATE; XANTHAN GUM; POLYACRYLATE CROSSPOLYMER-6; ALLANTOIN; ARGININE; C20-22 ALCOHOLS; SODIUM HYALURONATE; DIPOTASSIUM GLYCYRRHIZATE; BUTYLENE GLYCOL; GLYCERIN; CAPRYLIC/CAPRIC TRIGLYCERIDE; SIMMONDSIA CHINENSIS (JOJOBA) SEED OIL; SQUALANE; 1,2-HEXANEDIOL; HYDROXYACETOPHENONE; HYDROXYETHYLPIPERAZINE ETHANE SULFONIC ACID; TOCOPHEROL

84148-011

Active Ingredient(s)

WATER 78.894%

3-o-ETHYL ASCORBIC ACID 8%

PORTULACA OLERACEA EXTRACT 0.07%

LAVANDULA ANGUSTIFOLIA (LAVENDER) OIL 0.03%

SAURURUS CHINENSIS LEAF/ROOT EXTRACT 0.01%

TARAXACUM OFFICINALE (DANDELION) LEAF EXTRACT 0.01%

STEPHANIA TETRANDRA EXTRACT 0.002%

Purpose

Brighten and restore skin vitality

Use

After cleansing and toning, apply 2-3 drops of VC Essence to the face and neck.
Gently pat until fully absorbed, Use morning and night for optima| results.

Warnings

For external use only. Avoid contact with eyes. Discontinue use if irritation
occurs. Keep out of reach of children. Store in a cool, dry place away from direct
sunlight.

Do not use

If there is any irritation, please stop using immediately

WHEN USING

When Using Section: When using this product, avoid contact with eyes. If contact occurs,
rinse thoroughly with water. Discontinve use if any irritation or adverse reaction occurs.

Keep out of reach of children.

Directions

After cleansing and toning, apply 2-3 drops of VC Essence to the face and neck.
Gently pat until fully absorbed, Use morning and night for optimal results.

Other information

Store in a cool and dry place, away from direct sunlight

Inactive ingredients

C20-22 ALKYL PHOSPHATE，XANTHAN GUM，POLYACRYLATE CROSSPOLYMER-6，ALLANTOIN，ARGININE，

C20-22 ALCOHOLS，SODIUM HYALURONATE，DIPOTASSIUM GLYCYRRHIZATE，BUTYLENE GLYCOL，GLYCERIN，

CAPRYLIC/CAPRIC TRIGLYCERIDE，SIMMONDSIA CHINENSIS (JOJOBA) SEED OIL，SQUALANE，1,2-HEXANEDIOL，

HYDROXYACETOPHENONE，HYDROXYETHYLPIPERAZINE ETHANE SULFONIC ACID，TOCOPHEROL